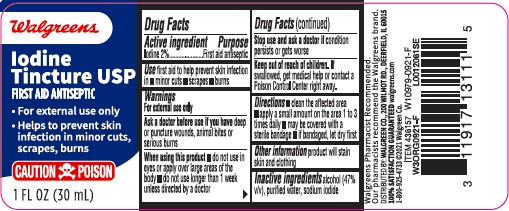 DRUG LABEL: Iodine
NDC: 0363-0088 | Form: LIQUID
Manufacturer: Walgreen Co.
Category: otc | Type: HUMAN OTC DRUG LABEL
Date: 20260212

ACTIVE INGREDIENTS: IODINE 20 mg/1 mL
INACTIVE INGREDIENTS: ALCOHOL; WATER; SODIUM IODIDE

Walgreens 088.000/088AA
Iodine Tincture

Active Ingredient

Iodine 2%

Purpose

First aid antiseptic

Use

First aid to help prevent skin infection in

- minor cuts
- scrapes
- burns

Warnings

For external use only

Ask a doctor before use

if you have deep or puncture wounds, animal bites or serious burns.

When using this product

- do not use in eyes or apply over large areas of the body
- do not use longer than 1 week unless directed by a doctor

Stop use and ask a doctor if

condition persists or gets worse

Keep out of reach of children.

If swallowed, get medical help or contact a Poison Control Center right away.

Directions

- clean the affected area
- apply a small amount on the area 1 to 3 times daily
- may be covered with a sterile bandage
- if bandaged, let dry first

Other information

product will stain skin and clothing

Inactive ingredients

alcohol (47%v/v), purified water, sodium iodide

ADVERSE REACTION

Walgreen Pharmacist Recommended

Our Pharmacists recommend the Walgreens brand.

Distributed by: Walgreen Co. 200 Wilmot Rd., Deerfield, IL 60015

100% satisfaction guaranteed walgreens.com

1-800-925-4733 2021 Walgreen Co.

principal display panel

Walgreens

Iodine tincture USP

First aid antiseptic

- For external use only
- Helps to prevent skin infection in minor cuts, scrapes, burns

CAUTION: POISON

1 FL OZ (30 mL)